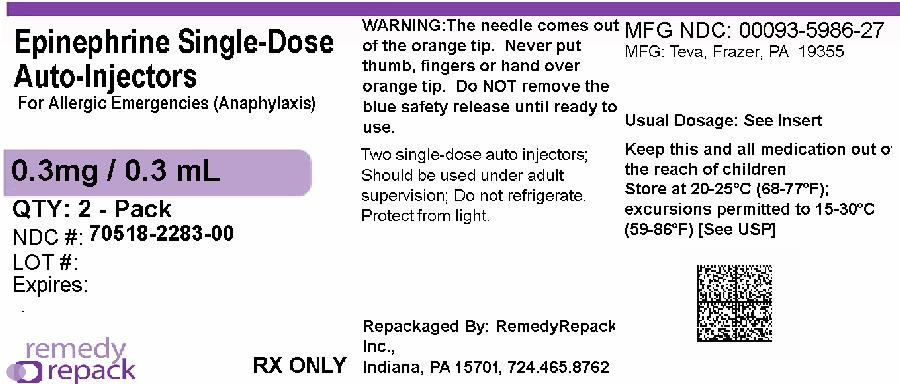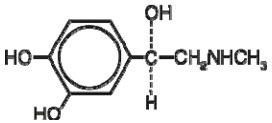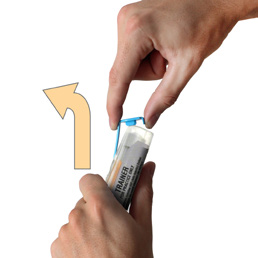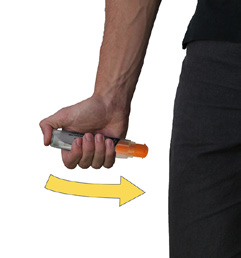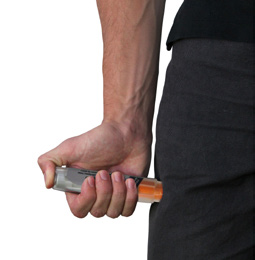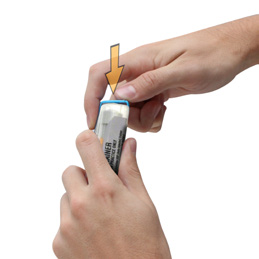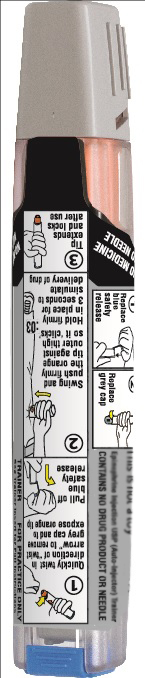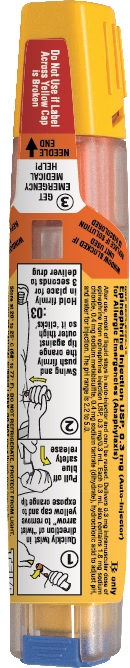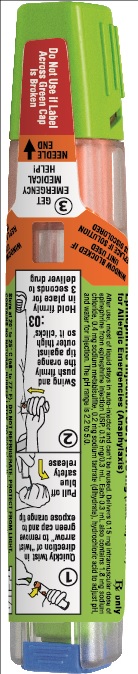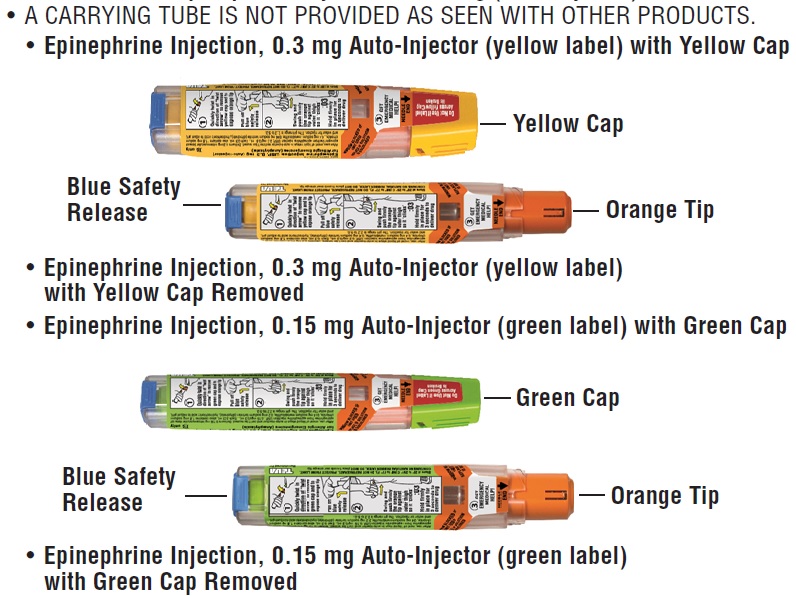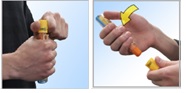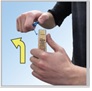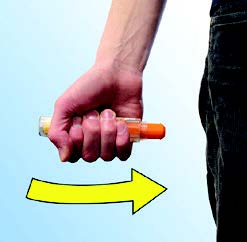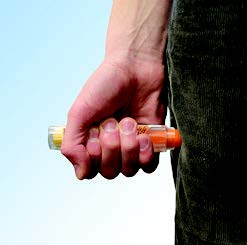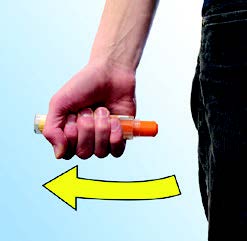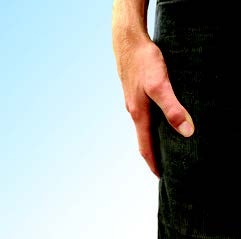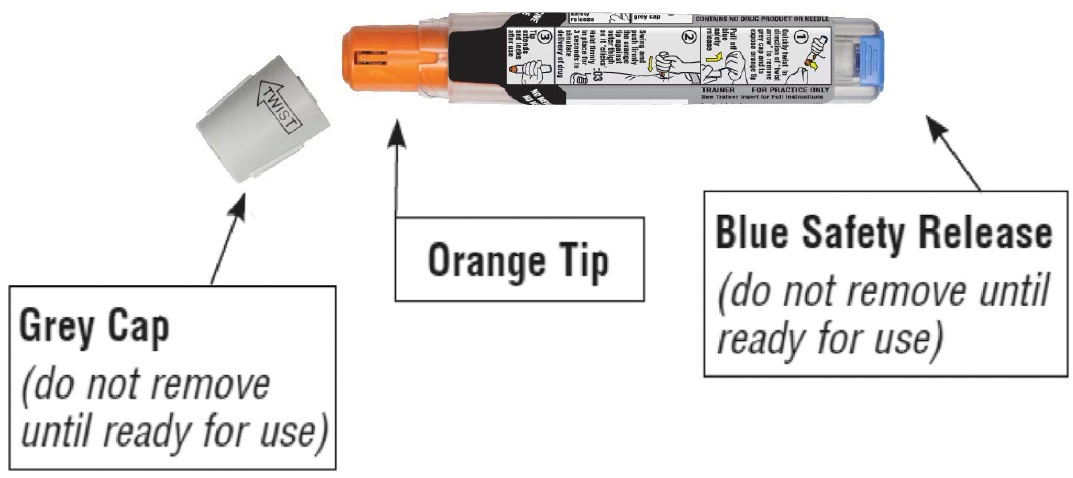 DRUG LABEL: Epinephrine
NDC: 70518-2283 | Form: INJECTION
Manufacturer: REMEDYREPACK INC.
Category: prescription | Type: HUMAN PRESCRIPTION DRUG LABEL
Date: 20260203

ACTIVE INGREDIENTS: EPINEPHRINE 0.3 mg/0.3 mL
INACTIVE INGREDIENTS: SODIUM CHLORIDE; SODIUM METABISULFITE; SODIUM TARTRATE DIHYDRATE; HYDROCHLORIC ACID; WATER

HIGHLIGHTS OF PRESCRIBING INFORMATION

These highlights do not include all the information needed to use EPINEPHRINE INJECTION, 0.3 mg and EPINEPHRINE INJECTION, 0.15 mg safely and effectively. See full prescribing information for EPINEPHRINE INJECTION, 0.3 mg and EPINEPHRINE INJECTION, 0.15 mg.
EPINEPHRINE injection, 0.3 mg, for intramuscular or subcutaneous use
EPINEPHRINE injection, 0.15 mg, for intramuscular or subcutaneous use
Initial U.S. Approval: 1939

1 INDICATIONS AND USAGE

Epinephrine Injection, 0.3 mg and Epinephrine Injection, 0.15 mg contain epinephrine, are non-selective alpha and beta-adrenergic receptor agonist indicated in the emergency treatment of allergic reactions (Type I) including anaphylaxis. (1)

2 DOSAGE AND ADMINISTRATION

- Patients greater than or equal to 30 kg (66 lbs): Epinephrine injection, 0.3 mg (2)
- Patients 15 to 30 kg (33 lbs to 66 lbs): Epinephrine injection, 0.15 mg (2)

Inject intramuscularly or subcutaneously into the anterolateral aspect of the thigh, through clothing if necessary. Each device is a single-dose injection. (2)

3 DOSAGE FORMS AND STRENGTHS

- Injection: 0.3 mg (0.3 mg/0.3 mL) single-dose pre-filled auto-injector

4 CONTRAINDICATIONS

None (4)

5 WARNINGS AND PRECAUTIONS

- In conjunction with use, seek immediate medical or hospital care. (5.1)
- Do not inject intravenously, into buttock, or into digits, hands, or feet. (5.2)
- To minimize the risk of injection related injury, hold the child’s leg firmly in place and limit movement prior to and during injection when administering to young children. (5.2)
- Rare cases of serious skin and soft tissue infections have been reported following epinephrine injection. Advise patients to seek medical care if they develop signs or symptoms of infection. (5.3)
- The presence of a sulfite in this product should not deter use. (5.4)
- Administer with caution in patients with heart disease; may aggravate angina pectoris or produce ventricular arrhythmias. (5.5)

6 ADVERSE REACTIONS

Adverse reactions to epinephrine include anxiety, apprehensiveness, restlessness, tremor, weakness, dizziness, sweating, palpitations, pallor, nausea and vomiting, headache, and/or respiratory difficulties. (6)

To report SUSPECTED ADVERSE REACTIONS, contact Teva Pharmaceuticals USA, Inc. at 1-888-838-2872 or FDA at 1-800-FDA-1088 or www.fda.gov/medwatch.

7 DRUG INTERACTIONS

- Cardiac glycosides or diuretics: observe for development of cardiac arrhythmias. (7)
- Tricyclic antidepressants, monoamine oxidase inhibitors, levothyroxine sodium, and certain antihistamines potentiate effects of epinephrine. (7)
- Beta-adrenergic blocking drugs antagonize cardiostimulating and bronchodilating effects of epinephrine. (7)
- Alpha-adrenergic blocking drugs antagonize vasoconstricting and hypertensive effects of epinephrine. (7)
- Ergot alkaloids may reverse the pressor effects of epinephrine. (7)

8 USE IN SPECIFIC POPULATIONS

- Elderly patients may be at greater risk of developing adverse reactions. (5.5, 8.5)

FULL PRESCRIBING INFORMATION

1 INDICATIONS AND USAGE

Epinephrine Injection, 0.3 mg and Epinephrine Injection, 0.15 mg are indicated in the emergency treatment of allergic reactions (Type I) including anaphylaxis to stinging insects (e.g., order Hymenoptera, which include bees, wasps, hornets, yellow jackets and fire ants) and biting insects (e.g., triatoma, mosquitoes), allergen immunotherapy, foods, drugs, diagnostic testing substances (e.g., radiocontrast media) and other allergens, as well as idiopathic anaphylaxis or exercise-induced anaphylaxis.

Epinephrine Injection, 0.3 mg and Epinephrine Injection, 0.15 mg are intended for immediate administration in patients who are determined to be at increased risk for anaphylaxis, including individuals with a history of anaphylactic reactions.

Anaphylactic reactions may occur within minutes after exposure and consist of flushing, apprehension, syncope, tachycardia, thready or unobtainable pulse associated with a fall in blood pressure, convulsions, vomiting, diarrhea and abdominal cramps, involuntary voiding, wheezing, dyspnea due to laryngeal spasm, pruritus, rashes, urticaria or angioedema.

Epinephrine Injection, 0.3 mg and Epinephrine Injection, 0.15 mg are intended for immediate administration as emergency supportive therapy only and are not a substitute for immediate medical care.

2 DOSAGE AND ADMINISTRATION

2.1 Recommended Dosage According to Patient Body Weight

- Patients greater than or equal to 30 kg (approximately 66 pounds or more): Epinephrine injection, 0.3 mg
- Patients 15 kg to 30 kg (33 pounds to 66 pounds): Epinephrine injection, 0.15 mg

2.2 Administration Instructions

- Inject the single-dose epinephrine injection, 0.3 mg or epinephrine injection, 0.15 mg intramuscularly or subcutaneously into the anterolateral aspect of the thigh, through clothing if necessary. Do not inject intravenously, and do not inject into buttocks, into digits, hands or feet [see Warnings and Precautions (5.2)].
- Instruct caregivers of young children who are prescribed an epinephrine injection, 0.3 mg or epinephrine injection, 0.15 mg and who may be uncooperative and kick or move during an injection to hold the leg firmly in place and limit movement prior to and during an injection [ see Warnings and Precautions (5.2)].
- Each epinephrine injection, 0.3 mg or epinephrine injection, 0.15 mg is a single-dose epinephrine injection for single use. Since the doses of epinephrine delivered from epinephrine injection, 0.3 mg or epinephrine injection, 0.15 mg are fixed, consider using other forms of injectable epinephrine if doses lower than 0.15 mg are deemed necessary.
- With severe persistent anaphylaxis, repeat injections with an additional epinephrine injection, 0.3 mg or epinephrine injection, 0.15 mg may be necessary. More than two sequential doses of epinephrine should only be administered under direct medical supervision [ see Warnings and Precautions (5.1)].
- The epinephrine solution in the clear window of the Epinephrine Injection 0.3 mg (Auto-Injector) or Epinephrine Injection 0.15 mg (Auto-Injector) should be inspected visually for particulate matter and discoloration.

Discarding After Use:

The epinephrine injection 0.3 mg and epinephrine injection 0.15 mg each contain 1 mL epinephrine solution. Approximately 0.7 mL remains in the auto-injector after activation, but is not available for future use, and should be discarded.

3 DOSAGE FORMS AND STRENGTHS

- Injection: 0.3 mg (0.3 mg/0.3 mL), clear and colorless solution in single-dose pre-filled auto-injector

4 CONTRAINDICATIONS

None

5 WARNINGS AND PRECAUTIONS

5.1 Emergency Treatment

Epinephrine injection, 0.3 mg and epinephrine injection, 0.15 mg are intended for immediate administration as emergency supportive therapy and are not intended as a substitute for immediate medical care. In conjunction with the administration of epinephrine, the patient should seek immediate medical or hospital care.More than two sequential doses of epinephrine should only be administered under direct medical supervision [ see Indications and Usage (1), Dosage and Administration (2) and Patient Counseling Information (17) ].

5.2 Injection-Related Complications

Epinephrine injection, 0.3 mg and epinephrine injection, 0.15 mg should onlybe injected into the anterolateral aspect of the thigh [ see Dosage and Administration (2) and Patient Counseling Information (17) ].

Do not inject intravenously
Large doses or accidental intravenous injection of epinephrine may result in cerebral hemorrhage due to sharp rise in blood pressure. Rapidly acting vasodilators can counteract the marked pressor effects of epinephrine if there is such inadvertent administration.

Do not inject into buttock
Injection into the buttock may not provide effective treatment of anaphylaxis. Advise the patient to go immediately to the nearest emergency room for further treatment of anaphylaxis. Additionally, injection into the buttock has been associated with Clostridial infections (gas gangrene). Cleansing with alcohol does not kill bacterial spores, and therefore, does not lower this risk.

Do not inject into digits, hands or feet
Since epinephrine is a strong vasoconstrictor, accidental injection into the digits, hands or feet may result in loss of blood flow to the affected area. Advise the patient to go immediately to the nearest emergency room and to inform the healthcare provider in the emergency room of the location of the accidental injection. Treatment of such inadvertent administration should consist of vasodilation, in addition to further appropriate treatment of anaphylaxis [ see Adverse Reactions (6)].

Hold leg firmly during injection
Lacerations, bent needles, and embedded needles have been reported when epinephrine injection, 0.3 mg and epinephrine injection, 0.15 mg have been injected into the thigh of young children who are uncooperative and kick or move during an injection. To minimize the risk of injection related injury when administering, hold the child’s leg firmly in place and limit movement prior to and during injection.

5.3 Serious Infections at the Injection Site

Rare cases of serious skin and soft tissue infections, including necrotizing fasciitis and myonecrosis caused by Clostridia (gas gangrene), have been reported at the injection site following epinephrine injection for anaphylaxis. Clostridiumspores can be present on the skin and introduced into the deep tissue with subcutaneous or intramuscular injection. While cleansing with alcohol may reduce presence of bacteria on the skin, alcohol cleansing does not kill Clostridiumspores. To decrease the risk of Clostridiuminfection, do not inject epinephrine injection into the buttock [ see Warnings and Precautions (5.2)]. Advise patients to seek medical care if they develop signs or symptoms of infection, such as persistent redness, warmth, swelling, or tenderness, at the epinephrine injection site.

5.4 Allergic Reactions Associated with Sulfite

The presence of a sulfite in this product should not deter administration of the drug for treatment of serious allergic or other emergency situations even if the patient is sulfite-sensitive.

Epinephrine is the preferred treatment for serious allergic reactions or other emergency situations even though this product contains sodium metabisulfite, a sulfite that may, in other products, cause allergic-type reactions including anaphylactic symptoms or life-threatening or less severe asthmatic episodes in certain susceptible persons.

The alternatives to using epinephrine in a life-threatening situation may not be satisfactory.

5.5 Disease Interactions

Some patients may be at greater risk for developing adverse reactions after epinephrine administration. Despite these concerns, it should be recognized that the presence of these conditions is not a contraindication to epinephrine administration in an acute, life-threatening situation. Therefore, patients with these conditions, and/or any other person who might be in a position to administer epinephrine injection, 0.3 mg or epinephrine injection, 0.15 mg to a patient experiencing anaphylaxis should be carefully instructed in regard to the circumstances under which epinephrine should be used.

Patients with Heart Disease

Epinephrine should be administered with caution to patients who have heart disease, including patients with cardiac arrhythmias, coronary artery or organic heart disease, or hypertension .In such patients, or in patients who are on drugs that may sensitize the heart to arrhythmias ,epinephrine may precipitate or aggravate angina pectoris as well as produce ventricular arrhythmias [ see Drug Interactions (7) and Adverse Reactions (6)].

Other Patients and Diseases

Epinephrine should be administered with caution to patients with hyperthyroidism, diabetes, elderly individuals, and pregnant women. Patients with Parkinson’s disease may notice a temporary worsening of symptoms.

6 ADVERSE REACTIONS

Due to the lack of randomized, controlled clinical trials of epinephrine for the treatment of anaphylaxis, the true incidence of adverse reactions associated with the systemic use of epinephrine is difficult to determine. Adverse reactions reported in observational trials, case reports, and studies are listed below.

Common adverse reactions to systemically administered epinephrine include anxiety; apprehensiveness; restlessness; tremor; weakness; dizziness; sweating; palpitations; pallor; nausea and vomiting; headache; and/or respiratory difficulties. These symptoms occur in some persons receiving therapeutic doses of epinephrine, but are more likely to occur in patients with hypertension or hyperthyroidism [ see Warnings and Precautions (5.5) ].

Cardiovascular Reactions

- Arrhythmias, including fatal ventricular fibrillation, have been reported, particularly in patients with underlying cardiac disease or those receiving certain drugs [ see Warnings and Precautions (5.5) and Drug Interactions (7) ].
- Rapid rises in blood pressure have produced cerebral hemorrhage, particularly in elderly patients with cardiovascular disease [ see Warnings and Precautions (5.5) ].
- Angina may occur in patients with coronary artery disease [ see Warnings and Precautions (5.5) ].
- Rare cases of stress cardiomyopathy have been reported in patients treated with epinephrine.

Reactions from Accidental Injection and/or Improper Technique

- Accidental injection into the digits, hands or feet may result in loss of blood flow to the affected area [ see Warnings and Precautions (5.2) ].
- Adverse reactions experienced as a result of accidental injections may include increased heart rate, local reactions including injection site pallor, coldness and hypoesthesia or injury at the injection site resulting in bruising, bleeding, discoloration, erythema or skeletal injury.
- Lacerations, bent needles, and embedded needles have been reported when epinephrine injection has been injected into the thigh of young children who are uncooperative and kick or move during the injection [ see Warnings and Precautions (5.2) ].
- Injection into the buttock has resulted in cases of gas gangrene [ see Warnings and Precautions (5.2) ].

Skin and Soft Tissue Infections

- Rare cases of serious skin and soft tissue infections, including necrotizing fasciitis and myonecrosis caused by Clostridia (gas gangrene), have been reported following epinephrine injection, including epinephrine injection 0.3 mg, in the thigh [ see Warnings and Precautions (5.3) ].

7 DRUG INTERACTIONS

Cardiac Glycosides, Diuretics, and Anti-arrhythmics

Patients who receive epinephrine while concomitantly taking cardiac glycosides, diuretics, or anti-arrhythmics should be observed carefully for the development of cardiac arrhythmias [ see Warnings and Precautions (5.5) ].

Antidepressants, Monoamine Oxidase Inhibitors, Levothyroxine, and Antihistamines

The effects of epinephrine may be potentiated by tricyclic antidepressants, monoamine oxidase inhibitors, levothyroxine sodium, and certain antihistamines, notably chlorpheniramine, tripelennamine, and diphenhydramine.

Beta-Adrenergic Blockers

The cardiostimulating and bronchodilating effects of epinephrine are antagonized by beta-adrenergic blocking drugs, such as propranolol.

Alpha-Adrenergic Blockers

The vasoconstricting and hypertensive effects of epinephrine are antagonized by alpha-adrenergic blocking drugs, such as phentolamine.

Ergot Alkaloids

Ergot alkaloids may also reverse the pressor effects of epinephrine.

8 USE IN SPECIFIC POPULATIONS

8.1 Pregnancy

Risk Summary

There are no adequate and well controlled studies of the acute effect of epinephrine in pregnant women. In animal reproductive studies, epinephrine administered by the subcutaneous route to rabbits, mice, and hamsters during the period of organogenesis was teratogenic at doses 7 times and higher than the maximum recommended human intramuscular and subcutaneous dose on a mg/m^2basis. Epinephrine is the first-line medication of choice for the treatment of anaphylaxis during pregnancy in humans. Epinephrine should be used for treatment of anaphylaxis during pregnancy in the same manner as it is used in non-pregnant patients.

In the U.S. general population, the estimated background risk of major birth defects and miscarriage in clinically recognized pregnancies is 2% to 4% and 15% to 20%, respectively.

Clinical Considerations

Disease-associated maternal and embryo/fetal risk:

During pregnancy, anaphylaxis can be catastrophic and can lead to hypoxic-ischemic encephalopathy and permanent central nervous system damage or death in the mother and, more commonly, in the fetus or neonate. The prevalence of anaphylaxis occurring during pregnancy is reported to be approximately 3 cases per
100,000 deliveries.

Management of anaphylaxis during pregnancy is similar to management in the general population. Epinephrine is the first line-medication of choice for treatment of anaphylaxis; it should be used in the same manner in pregnant and non-pregnant patients. In conjunction with the administration of epinephrine, the patient should seek immediate medical or hospital care.

Data

Animal Data:

In an embryofetal development study with rabbits dosed during the period of organogenesis, epinephrine was shown to be teratogenic (including gastroschisis and embryonic lethality) at doses approximately 40 times the maximum recommended intramuscular or subcutaneous dose (on a mg/m^2basis at a maternal subcutaneous dose of 1.2 mg/kg/day for two to three days).

In an embryofetal development study with mice dosed during the period of organogenesis, epinephrine was shown to be teratogenic (including embryonic lethality) at doses approximately 8 times the maximum recommended intramuscular or subcutaneous dose (on a mg/m^2basis at maternal subcutaneous dose of 1 mg/kg/day for 10 days). These effects were not seen in mice at approximately 4 times the maximum recommended daily intramuscular or subcutaneous dose (on a mg/m^2basis at a subcutaneous maternal dose of 0.5 mg/kg/day for 10 days).

In an embryofetal development study with hamsters dosed during the period of organogenesis from gestation days 7 to 10, epinephrine was shown to be teratogenic at doses approximately 7 times the maximum recommended intramuscular or subcutaneous dose (on a mg/m^2basis at a maternal subcutaneous dose of 0.5 mg/kg/day).

8.2 Lactation

Risk Summary

There is no information on the presence of epinephrine in human milk, the effects on breastfed infants, or the effects on milk production. Epinephrine is the first line-medication of choice for treatment of anaphylaxis; it should be used in the same manner in breastfeeding and non-breastfeeding patients.

8.4 Pediatric Use

Epinephrine injection, 0.3 mg or epinephrine injection, 0.15 mg may be administered to pediatric patients at a dosage appropriate to body weight [ see Dosage and Administration (2.1) ] .Clinical experience with the use of epinephrine suggests that the adverse reactions seen in children are similar in nature and extent to those both expected and reported in adults. Since the doses of epinephrine delivered from epinephrine injection, 0.3 mg and epinephrine injection, 0.15 mg are fixed, consider using other forms of injectable epinephrine if doses lower than 0.15 mg are deemed necessary.

8.5 Geriatric Use

Clinical studies for the treatment of anaphylaxis have not been performed in subjects aged 65 and over to determine whether they respond differently from younger subjects. However, other reported clinical experience with use of epinephrine for the treatment of anaphylaxis has identified that geriatric patients may be particularly sensitive to the effects of epinephrine. Therefore, epinephrine injection, 0.3 mg should be administered with caution in elderly individuals, who may be at greater risk for developing adverse reactions after epinephrine administration [ see Warnings and Precautions (5.5), Overdosage (10) ].

10 OVERDOSAGE

Overdosage of epinephrine may produce extremely elevated arterial pressure, which may result in cerebrovascular hemorrhage, particularly in elderly patients. Overdosage may also result in pulmonary edema because of peripheral vascular constriction together with cardiac stimulation. Treatment consists of rapidly acting vasodilators or alpha-adrenergic blocking drugs and/or respiratory support.

Epinephrine overdosage can also cause transient bradycardia followed by tachycardia, and these may be accompanied by potentially fatal cardiac arrhythmias. Premature ventricular contractions may appear within one minute after injection and may be followed by multifocal ventricular tachycardia (prefibrillation rhythm). Subsidence of the ventricular effects may be followed by atrial tachycardia and occasionally by atrioventricular block. Treatment of arrhythmias consists of administration of a beta-adrenergic blocking drug such as propranolol.

Overdosage sometimes results in extreme pallor and coldness of the skin, metabolic acidosis, and kidney failure. Suitable corrective measures must be taken in such situations.

11 DESCRIPTION

Epinephrine Injection USP, 0.3 mg and Epinephrine Injection USP, 0.15 mg are single-dose auto-injectors and combination products containing drug and device components.

Each Epinephrine Injection USP, 0.3 mg (Auto-Injector) delivers a single dose of 0.3 mg epinephrine, USP from epinephrine injection USP, 0.3 mg/0.3 mL in a sterile solution.

Each Epinephrine Injection USP, 0.15 mg (Auto-Injector) delivers a single dose of 0.15 mg epinephrine, USP from epinephrine injection USP, 0.15 mg/0.3 mL in a sterile solution.

Each 0.3 mL in the Epinephrine Injection USP, 0.3 mg (Auto-Injector) contains 0.3 mg epinephrine USP, 1.8 mg sodium chloride, 0.4 mg sodium metabisulfite, 0.4 mg sodium tartrate (dihydrate), hydrochloric acid to adjust pH, and water for injection. The pH range is 2.2 to 5.0.

Each 0.3 mL in the Epinephrine Injection USP, 0.15 mg (Auto-Injector) contains 0.15 mg epinephrine USP, 1.8 mg sodium chloride, 0.4 mg sodium metabisulfite, 0.2 mg sodium tartrate (dihydrate), hydrochloric acid to adjust pH, and water for injection. The pH range is 2.2 to 5.0.

Epinephrine, USP is a sympathomimetic catecholamine. Chemically, epinephrine, USP is (-)-3,4-Dihydroxy-α-[(methylamino)methyl]benzyl alcohol with the following structure:

Epinephrine solution deteriorates rapidly on exposure to air or light, turning pink from oxidation to adrenochrome and brown from the formation of melanin. Replace Epinephrine Injection USP, 0.3 mg and Epinephrine Injection USP, 0.15 mg if the epinephrine solution appears discolored (pinkish or darker than slightly yellow), cloudy, or if it contains a precipitate.

Thoroughly review the patient instructions and operation of Epinephrine Injection USP, 0.3 mg or Epinephrine Injection USP, 0.15 mg with patients and caregivers prior to use [ see Patient Counseling Information (17) ].

12 CLINICAL PHARMACOLOGY

12.1 Mechanism of Action

Epinephrine acts on both alpha- and beta-adrenergic receptors.

12.2 Pharmacodynamics

Through its action on alpha-adrenergic receptors, epinephrine lessens the vasodilation and increased vascular permeability that occurs during anaphylaxis, which can lead to loss of intravascular fluid volume and hypotension.

Through its action on beta-adrenergic receptors, epinephrine causes bronchial smooth muscle relaxation and helps alleviate bronchospasm, wheezing and dyspnea that may occur during anaphylaxis.

Epinephrine also alleviates pruritus, urticaria, and angioedema and may relieve gastrointestinal and genitourinary symptoms associated with anaphylaxis because of its relaxer effects on the smooth muscle of the stomach, intestine, uterus and urinary bladder.

When given subcutaneously or intramuscularly, epinephrine has a rapid onset and short duration of action.

13 NONCLINICAL TOXICOLOGY

13.1 Carcinogenesis, Mutagenesis, Impairment of Fertility

Long-term studies to evaluate the carcinogenic potential of epinephrine have not been conducted.

Epinephrine and other catecholamines have been shown to have mutagenic potential in vitro. Epinephrine was positive in the Salmonellabacterial reverse mutation assay, positive in the mouse lymphoma assay, and negative in the in vivomicronucleus assay. Epinephrine is an oxidative mutagen based on the E. coliWP2 Mutoxitest bacterial reverse mutation assay. This should not prevent the use of epinephrine where indicated [see Indications and Usage (1)].

The potential for epinephrine to impair reproductive performance has not been evaluated, but epinephrine has been shown to decrease implantation in female rabbits dosed subcutaneously with 1.2 mg/kg/day (40-fold the highest human intramuscular or subcutaneous daily dose) during gestation days 3 to 9.

16 HOW SUPPLIED/STORAGE AND HANDLING

Epinephrine Injection USP, 0.3 mg (Auto-Injectors) is supplied with two single-dose pre-filled auto-injectors and one auto-injector trainer device: 0.3 mg/0.3 mL

NDC: 70518-2283-0

PACKAGING: 2 in 1 CARTON, 1 in 1 CONTAINER, 0.3 mL in 1 SYRINGE TYPE 2

Storage and Handling

Protect from light. Epinephrine, USP is light sensitive and the auto-injector is manufactured from transparent UV stabilized polycarbonate to protect it from light.

Store at 20° to 25°C (68° to 77°F); excursions permitted to 15° to 30°C (59° to 86°F) [See USP Controlled Room Temperature].

Do not refrigerate.

Before using, check to make sure the solution in the auto-injector is clear and colorless.

Replace the auto-injector if the solution is discolored (pinkish or darker than slightly yellow), cloudy, or contains a precipitate.

Properly dispose all used, unwanted or expired epinephrine injection, 0.3 mg and epinephrine injection, 0.15 mg auto-injectors.

KEEP THIS AND ALL MEDICATIONS OUT OF THE REACH OF CHILDREN.

Repackaged and Distributed By:

Remedy Repack, Inc.

625 Kolter Dr. Suite #4 Indiana, PA 1-724-465-8762

17 PATIENT COUNSELING INFORMATION

See FDA-Approved Patient Labeling (Patient Information and Instructions for Use)

A healthcare provider should review the patient instructions and operation of epinephrine injection, 0.3 mg and epinephrine injection, 0.15 mg in detail, with the patient or caregiver.

Epinephrine is essential for the treatment of anaphylaxis. Patients who are at risk of or with a history of severe allergic reactions (anaphylaxis) to insect stings or bites, foods, drugs, and other allergens, as well as idiopathic and exercise-induced anaphylaxis, should be carefully instructed about the circumstances under which epinephrine should be used.

Administration

Instruct patients and/or caregivers in the appropriate use of epinephrine injection, 0.3 mg and epinephrine injection, 0.15 mg should be injected into the middle of the outer thigh (through clothing, if necessary). Each device is a single-use injection. Advise patients to seek immediate medical care in conjunction with administration of epinephrine injection, 0.3 mg and epinephrine injection, 0.15 mg.

Instruct caregivers to hold the leg of young children firmly in place and limit movement prior to and during injection. Lacerations, bent needles, and embedded needles have been reported when epinephrine injection, 0.3 mg and epinephrine injection, 0.15 mg have been injected into the thigh of young children who are uncooperative and kick or move during an injection [ see Warnings and Precautions (5.2)].

Instruct patients and/or caregivers to throw away the blue safety release immediately after using epinephrine injection, 0.3 mg and epinephrine injection, 0.15 mg. This small part may pose a choking hazard for children.

Complete patient information, including dosage, directions for proper administration and precautions can be found inside each epinephrine injection, 0.3 mg or epinephrine injection, 0.15 mg carton. A printed label on the surface of epinephrine injection, 0.3 mg and epinephrine injection, 0.15 mg shows instructions for use and a diagram depicting the injection process.

Training

Instruct patients and/or caregivers to use and practice with the Trainer to familiarize themselves with the use of epinephrine injection, 0.3 mg and epinephrine injection, 0.15 mg in an allergic emergency. The Trainer may be used multiple times. A Trainer device is provided in 2-Pack cartons.

Instruct patients and/or caregivers to immediately place the blue safety release back on the Trainer and reset it after practicing. This small part may pose a choking hazard for children.

Adverse Reactions

Epinephrine may produce symptoms and signs that include an increase in heart rate, the sensation of a more forceful heartbeat, palpitations, sweating, nausea and vomiting, difficulty breathing, pallor, dizziness, weakness or shakiness, headache, apprehension, nervousness, or anxiety. These signs and symptoms usually subside rapidly, especially with rest, quiet and recumbency. Patients with hypertension or hyperthyroidism may develop more severe or persistent effects, and patients with coronary artery disease could experience angina. Patients with diabetes may develop increased blood glucose levels following epinephrine administration. Patients with Parkinson’s disease may notice a temporary worsening of symptoms [ see Warnings and Precautions (5.5)].

Accidental Injection

Advise patients to seek immediate medical care in the case of accidental injection. Since epinephrine is a strong vasoconstrictor when injected into the digits, hands, or feet, treatment should be directed at vasodilatation if there is such an accidental injection to these areas [ see Warnings and Precautions (5.2)].

Serious Infections at the Injection Site

Rare cases of serious skin and soft tissue infections, including necrotizing fasciitis and myonecrosis caused by Clostridia (gas gangrene), have been reported at the injection site following epinephrine injection for anaphylaxis. Advise patients to seek medical care if they develop signs or symptoms of infection, such as persistent redness, warmth, swelling, or tenderness, at the epinephrine injection site [ see Warnings and Precautions (5.3)].

Storage and Handling

Instruct patients to inspect the epinephrine solution visually through the clear window of the auto-injector periodically. Replace epinephrine injection, 0.3 mg and epinephrine injection, 0.15 mg if the epinephrine solution appears discolored (pinkish or darker than slightly yellow), cloudy or if it contains a precipitate. Epinephrine is light sensitive and should be protected from light. The auto-injector is not waterproof. Instruct patients that epinephrine injection, 0.3 mg and epinephrine injection, 0.15 mg must be used or properly disposed once the blue safety release is removed or after use [ see Storage and Handling (16.2)].

Advise patients and caregivers to give used epinephrine injection, 0.3 mg and epinephrine injection, 0.15 mg auto-injectors to their healthcare provider for inspection and proper disposal.

Advise patients and caregivers to promptly dispose of medicines that are no longer needed. Dispose of expired, unwanted, or unused epinephrine injection, 0.3 mg and epinephrine injection, 0.15 mg auto-injectors in an FDA-cleared sharps container. Instruct patients not to dispose epinephrine injection, 0.3 mg or epinephrine injection, 0.15 mg in their household trash. Instruct patients that if they do not have a FDA-cleared sharps disposal container, they may use a household container that is made of a heavy-duty plastic, can be closed with a tight-fitting and puncture-resistant lid without sharps being able to come out, upright and stable during use, leak-resistant, and properly labeled to warn of hazardous waste inside the container. Inform patients that they can visit the FDA website for additional information on disposal of unused medicines.

Complete patient information, including dosage, directions for proper administration and precautions can be found inside each epinephrine injection, 0.3 mg (Auto-Injector) and epinephrine injection, 0.15 mg (Auto-Injector) carton.

Manufactured For:
Teva Pharmaceuticals USA, Inc.
North Wales, PA 19454

Rev. D 1/2021

Repackaged By / Distributed By: RemedyRepack Inc.

625 Kolter Drive, Indiana, PA 15701

(724) 465-8762

PATIENT INFORMATION and INSTRUCTIONS FOR USE

Epinephrine Injection USP, 0.3 mg (Auto-Injector)

Epinephrine Injection USP, 0.3 mg = one dose of 0.3 mg epinephrine USP, 0.3 mg/0.3 mL

Epinephrine Injection USP, 0.15 mg (Auto-Injector)

Epinephrine Injection USP, 0.15 mg = one dose of 0.15 mg epinephrine USP, 0.15 mg/0.3 mL

For allergic emergencies (anaphylaxis)

Patient Information

Read this Patient Information Leaflet carefully before using the epinephrine injection, 0.3 mg (auto-injector) or epinephrine injection, 0.15 mg (auto-injector) and each time you get a refill. There may be new information. You, your parent, caregiver, or others who may be in a position to administer epinephrine injection, 0.3 mg (auto-injector) or epinephrine injection, 0.15 mg (auto-injector), should know how to use it before you have an allergic emergency.

This information does not take the place of talking with your healthcare provider about your medical condition or your treatment.

What is the most important information I should know about epinephrine injection, 0.3 mg and epinephrine injection, 0.15 mg?

1. Epinephrine injection, 0.3 mg and epinephrine injection, 0.15 mg are single-dose automatic injection devices (auto-injectors) that contain epinephrine, a medicine used to treat allergic emergencies (anaphylaxis). Anaphylaxis can be life threatening, can happen within minutes, and can be caused by stinging and biting insects, allergy injections, foods, medicines, exercise, or unknown causes.

Symptoms of anaphylaxis may include:

- trouble breathing
- wheezing
- hoarseness (changes in the way your voice sounds)
- hives (raised reddened rash that may itch)
- severe itching
- swelling of your face, lips, mouth, or tongue
- skin rash, redness, or swelling
- fast heartbeat
- weak pulse
- feeling very anxious
- confusion
- stomach pain
- losing control of urine or bowel movements (incontinence)
- diarrhea or stomach cramps
- dizziness, fainting, or “passing out” (unconsciousness)

2. Always carry your epinephrine injection, 0.3 mg or epinephrine injection, 0.15 mg with you because you may not know when anaphylaxis may happen.
Talk to your healthcare provider if you need additional units to keep at work, school, or other locations. Tell your family members, caregivers, and others where you keep your epinephrine injection, 0.3 mg or epinephrine injection, 0.15 mg and how to use it before you need it. You may be unable to speak in an allergic emergency.

3. When you have an allergic emergency (anaphylaxis)

- Use epinephrine injection, 0.3 mg or epinephrine injection, 0.15 mg right away.
- Get emergency medical help right away. You may need further medical attention. You may need to use a second epinephrine injection, 0.3 mg or epinephrine injection, 0.15 mg if symptoms continue or recur. Only a healthcare provider should give additional doses of epinephrine if you need more than 2 injections for a single anaphylaxis episode.

What are epinephrine injection, 0.3 mg and epinephrine injection, 0.15 mg?

- Epinephrine injection, 0.3 mg and epinephrine injection, 0.15 mg are disposable, pre-filled auto-injectors used to treat life-threatening, allergic emergencies including anaphylaxis in people who are at risk for or have a history of serious allergic emergencies. Each device contains a single dose of epinephrine.
- Epinephrine injection, 0.3 mg and epinephrine injection, 0.15 mg are for immediate self (or caregiver) administration and do not take the place of emergency medical care. You should get emergency help right away after using epinephrine injection, 0.3 mg and epinephrine injection, 0.15 mg.
- Epinephrine injection, 0.3 mg and epinephrine injection, 0.15 mg are for people who have been prescribed this medicine by their healthcare provider.
- The Epinephrine Injection, 0.3 mg (Auto-Injector) is for patients who weigh 66 pounds or more (30 kilograms or more).
- The Epinephrine Injection, 0.15 mg (Auto-Injector) is for patients who weigh about 33 to 66 pounds (15 to 30 kilograms).
- It is not known if epinephrine injection, 0.3 mg and epinephrine injection, 0.15 mg are safe and effective in children who weigh less than 33 pounds (15 kilograms).

What should I tell my healthcare provider before using the epinephrine injection, 0.3 mg or epinephrine injection, 0.15 mg?

Before you use epinephrine injection, 0.3 mg or epinephrine injection, 0.15 mg, tell your healthcare provider about all your medical conditions, but especially if you:

- have heart problems or high blood pressure.
- have diabetes.
- have thyroid problems.
- have asthma.
- have a history of depression.
- have Parkinson’s disease.
- are pregnant or plan to become pregnant. It is not known if epinephrine will harm your unborn baby.
- are breastfeeding or plan to breastfeed. It is not known if epinephrine passes into your breast milk.

Tell your healthcare provider about all the medicines you take, including prescription and over-the-counter medicines, vitamins, and herbal supplements. Tell your healthcare provider about all of your known allergies.

Especially tell your healthcare provider if you take certain asthma medicines.

Epinephrine injection, 0.3 mg or epinephrine injection, 0.15 mg and other medicines may affect each other, causing side effects. Epinephrine injection, 0.3 mg or epinephrine injection, 0.15 mg may affect the way other medicines work, and other medicines may affect how epinephrine injection, 0.3 mg or epinephrine injection, 0.15 mg work.

Know the medicines you take. Keep a list of them to show your healthcare provider and pharmacist when you get a new medicine.

Use your epinephrine injection, 0.3 mg or epinephrine injection, 0.15 mg for treatment of anaphylaxis as prescribed by your healthcare provider, regardless of your medical conditions or the medicines you take.

How should I use epinephrine injection, 0.3 mg and epinephrine injection, 0.15 mg?

- Each epinephrine injection, 0.3 mg (auto-injector) or epinephrine injection, 0.15 mg (auto-injector) contains only 1 dose of medicine (single-dose).
- Epinephrine injection, 0.3 mg and epinephrine injection, 0.15 mg Auto-Injectors deliver a fixed dose of epinephrine. The auto-injectors cannot be reused. Do not try to reuse epinephrine injection, 0.3 mg or epinephrine injection, 0.15 mg after the device has been activated. It is normal for most of the medicine to remain in the auto-injector after the dose has been injected. The dose has been injected if the orange tip is extended and the window is blocked.
- Epinephrine injection, 0.3 mg or epinephrine injection, 0.15 mg should be injected into the middle of your outer thigh (upper leg). It can be injected through your clothing if needed. Do not inject into a vein or into the buttocks, fingers, toes, hands or feet.
- Read the Instructions for Use at the end of this Patient Information Leaflet about the right way to use epinephrine injection, 0.3 mg or epinephrine injection, 0.15 mg.
- Your healthcare provider will show you how to safely use the epinephrine injection, 0.3 mg (auto-injector) or epinephrine injection, 0.15 mg (auto-injector).
- Use your single-dose epinephrine injection, 0.3 mg or epinephrine injection, 0.15 mg exactly as your healthcare provider tells you to use it. You may need to use a second epinephrine injection, 0.3 mg or epinephrine injection, 0.15 mg if symptoms continue or recur. Only a healthcare provider should give additional doses of epinephrine if you need more than 2 injections for a single anaphylaxis episode.
- Caution: Never put your thumb, fingers, or hand over the orange tip. Never press or push the orange tip with your thumb, fingers, or hand.The needle comes out of the orange tip. Accidental injection into finger, hands or feet may cause a loss of blood flow to these areas. If an accidental injection happens, go immediately to the nearest emergency room.Tell the healthcare provider where on your body you received the accidental injection.
- Your epinephrine injection, 0.3 mg (auto-injector) and epinephrine injection, 0.15 mg (auto-injector) may come packaged with an Epinephrine Injection Trainer and separate Epinephrine Injection Trainer Instructions for Use. The Epinephrine Injection Trainer has a grey color. The grey Epinephrine Injection Trainer contains no medicine and no needle.Keep the Epinephrine Injection Trainer and the real Epinephrine Injection, 0.3 mg and Epinephrine Injection, 0.15 mg Auto-Injectors away from young children. The real Epinephrine Injection, 0.3 mg and Epinephrine Injection, 0.15 mg Auto-Injectors and Epinephrine Injection Trainer are not toys. For young children, use of the Epinephrine Injection Trainer and the real Epinephrine Injection, 0.3 mg and Epinephrine Injection, 0.15 mg Auto-Injectors should be supervised by an adult. Periodically practice with your Epinephrine Injection Trainer before an allergic emergency happens to make sure you are able to safely use the real epinephrine injection, 0.3 mg (auto-injector) and epinephrine injection, 0.15 mg (auto-injector) in an emergency. Always carry your real epinephrine injection, 0.3 mg (auto-injector) or epinephrine injection 0.15 mg (auto-injector) with you in case of an allergic emergency. Additional training resources are available at www.TevaEpinephrine.com.
- Do not drop the auto-injector. If the auto-injector is dropped, check for damage and leakage. Throw away (dispose of) the auto-injector and replace if damage or leakage is noticed or suspected.

What are the possible side effects of epinephrine injection, 0.3 mg and epinephrine injection, 0.15 mg?

Epinephrine injection, 0.3 mg and epinephrine injection, 0.15 mg may cause serious side effects.

- The epinephrine injection, 0.3 mg or epinephrine injection, 0.15 mg should only be injected into the middle of your outer thigh (upper leg). Do not inject the epinephrine injection, 0.3 mg or epinephrine injection, 0.15 mg into your:
  - veins
  - buttocks
  - fingers, toes, hands, or feet
    If you accidentally inject epinephrine injection, 0.3 mg or epinephrine injection, 0.15 mg into any other part of your body, go to the nearest emergency room right away. Tell the healthcare provider where on your body you received the accidental injection.
- Rarely, patients who have used epinephrine injection, 0.3 mg or epinephrine injection, 0.15 mg may develop infections at the injection site within a few days of an injection. Some of these infections can be serious. Call your healthcare provider right away if you have any of the following at an injection site:
  - redness that does not go away
  - swelling
  - tenderness
  - the area feels warm to the touch
- Cuts on the skin, bent needles, and needles that remain in the skin after the injection, have happened in young children who do not cooperate and kick or move during an injection. If you inject a young child with epinephrine injection, 0.3 mg or epinephrine injection, 0.15 mg, hold their leg firmly in place before and during the injection to prevent injuries. Ask your healthcare provider to show you how to:

1. Hold the young child firmly in place (restrain).
2. With 1 hand, quickly twist the yellow cap off the Epinephrine Injection, 0.3 mg auto-injector or the green cap off the Epinephrine Injection, 0.15 mg auto-injector in the direction of the “twist arrow” to remove it.
3. Grasp the auto-injector in your fist with the orange tip (needle end) pointing downward.
4. With your other hand, pull off the blue safety release.

- If you have certain medical conditions, or take certain medicines, your condition may get worse or you may have longer lasting side effects when you use your epinephrine injection, 0.3 mg or epinephrine injection, 0.15 mg. Talk to your healthcare provider about all your medical conditions.

Common side effects of epinephrine injection, 0.3 mg and epinephrine injection, 0.15 mg include:

- fast, irregular or “pounding” heartbeat
- sweating
- headache
- weakness
- shakiness
- paleness
- feelings of over excitement, nervousness or anxiety
- dizziness
- nausea or vomiting
- breathing problems

These side effects may go away with rest. Tell your healthcare provider if you have any side effect that bothers you or that does not go away.

These are not all the possible side effects of the epinephrine injection, 0.3 mg or epinephrine injection, 0.15 mg. For more information, ask your healthcare provider or pharmacist.

Call your doctor for medical advice about side effects. You may report side effects to FDA at 1-800-FDA-1088.

How should I store epinephrine injection, 0.3 mg and epinephrine injection, 0.15 mg?

- Store epinephrine injection, 0.3 mg and epinephrine injection, 0.15 mg at room temperature between 68° to 77°F (20° to 25°C).
- Protect from light.
- Do not expose to extreme cold or heat. For example, do not store in your vehicle’s glove box and do not store in the refrigerator or freezer.
- Examine the contents in the clear window of your auto-injector periodically. The solution should be clear. If the solution is discolored (pinkish or darker than slightly yellow) or contains solid particles, replace the unit.
- Always protect your epinephrine injection, 0.3 mg (auto-injector) and epinephrine injection, 0.15 mg (auto-injector) from damage and water.
- The blue safety release helps to prevent accidental injection. Keep the blue safety release on until you need to use epinephrine injection, 0.3 mg or epinephrine injection, 0.15 mg.
- Your epinephrine injection, 0.3 mg or epinephrine injection, 0.15 mg has an expiration date. Replace it before the expiration date. Throw away (dispose of) expired, unwanted, or unused epinephrine injection, 0.3 mg and epinephrine injection, 0.15 mg in an FDA-cleared sharps disposal container. Do not throw away the epinephrine injection, 0.3 mg or epinephrine injection, 0.15 mg in your household trash. If you do not have an FDA-cleared sharps disposal container, you may use a household container that is:
  - Made of heavy-duty plastic,
  - Can be closed with a tight-fitting, puncture-resistant lid, without sharps being able to come out,
  - Upright and stable during use,
  - Leak-resistant, and
  - Properly labeled to warn of hazardous waste inside the container.
  When your sharps disposal container is almost full, you will need to follow your community guidelines for the right way to dispose of your sharps disposal container. There may be state or local laws about how you should throw away used needles and syringes. For more information about safe sharps disposal, and for specific information about sharps disposal in the state that you live in, go to the FDA’s website at: http://www.fda.gov/safesharpsdisposal
  Visit the FDA’s website (https://www.fda.gov/drugs/safe-disposal-medicines/disposal-unused-medicines-what-you-should-know) for more information about how to throw away (dispose of) unused, unwanted or expired medicines.

Keep epinephrine injection, 0.3 mg and epinephrine injection, 0.15 mg and all medicines out of the reach of children.

General information about the safe and effective use of epinephrine injection, 0.3 mg and epinephrine injection, 0.15 mg

Medicines are sometimes prescribed for purposes other than those listed in a Patient Information Leaflet. Do not use the epinephrine injection, 0.3 mg or epinephrine injection, 0.15 mg for a condition for which it was not prescribed. Do not give your epinephrine injection, 0.3 mg or epinephrine injection, 0.15 mg to other people.

This Patient Information Leaflet summarizes the most important information about epinephrine injection, 0.3 mg and epinephrine injection, 0.15 mg. If you would like more information, talk to your healthcare provider. You can ask your pharmacist or healthcare provider for information about epinephrine injection, 0.3 mg and epinephrine injection, 0.15 mg that is written for health professionals.

For more information and video instructions on the use of epinephrine injection, 0.3 mg and epinephrine injection, 0.15 mg go to www.TevaEpinephrine.comor call 1-888-838-2872.

What are the ingredients in epinephrine injection, 0.3 mg and epinephrine injection, 0.15 mg?

Active Ingredients: Epinephrine

Inactive Ingredients: sodium chloride, sodium metabisulfite, sodium tartrate (dihydrate), hydrochloric acid, and water

Important Information

- The Epinephrine Injection, 0.3 mg (Auto-Injector) has a yellow colored label.
- The Epinephrine Injection, 0.15 mg (Auto-Injector) has a green colored label.
- The Epinephrine Injection Trainer has a grey color and contains no medicine and no needle.
- Your auto-injector is designed to work through clothing.
- The blue safety release on the Epinephrine Injection, 0.3 mg (Auto-Injector) and Epinephrine Injection, 0.15 mg (Auto-Injector) helps to prevent accidental injection of the device. Do not remove the blue safety release until you are ready to use it.
- Choking hazard: The blue safety release is a small part that may become a choking hazard for children. Throw away the blue safety release immediately after using epinephrine injection, 0.3 mg and epinephrine injection, 0.15 mg Auto-Injector.
- Only inject into the middle of the outer thigh (upper leg). Never inject into any other part of the body.
- Never put your thumb, fingers, or your hand over the orange tip. The needle comes out of the orange tip.
- If an accidental injection happens, get emergency medical help right away.

INSTRUCTIONS FOR USE

Epinephrine Injection USP, 0.3 mg (Auto-Injector)

Epinephrine Injection USP, 0.3 mg = one dose of 0.3 mg epinephrine USP, 0.3 mg/0.3 mL

Epinephrine Injection USP, 0.15 mg (Auto-Injector)

Epinephrine Injection USP, 0.15 mg = one dose of 0.15 mg epinephrine USP, 0.15 mg/0.3 mL

For allergic emergencies (anaphylaxis)

Read this Instructions for Use carefully before you use epinephrine injection, 0.3 mg or epinephrine injection, 0.15 mg. Before you need to use your single-dose epinephrine injection, 0.3 mg or epinephrine injection, 0.15 mg auto-injector, make sure your healthcare provider shows you the right way to use it. Parents, caregivers, and others who may be in a position to administer epinephrine injection, 0.3 mg (auto-injector) or epinephrine injection, 0.15 mg (auto-injector) should also understand how to use it as well. If you have any questions, ask your healthcare provider.

Your Epinephrine Injection, 0.3 mg (Auto-Injector) and Epinephrine Injection, 0.15 mg (Auto-Injector)

A dose of epinephrine injection, 0.3 mg or epinephrine injection, 0.15 mg requires 3 steps: Prepare, Administer and Get emergency medical help

Step 1. Prepare epinephrine injection, 0.3 mg or epinephrine injection, 0.15 mg for injection

Quickly twist the yellow cap off the epinephrine injection, 0.3 mg auto-injector or the green cap off the epinephrine injection, 0.15 mg auto-injector in the direction of the “twist arrow” to remove it.

Grasp the auto-injector in your fist with the orange tip (needle end) pointing downward.With your other hand, pull off the blue safety release.

Important: The blue safety release is a small part that may become a choking hazard for children. Throw away the blue safety release immediately after usingepinephrine injection,0.3 mg or epinephrine injection,0.15 mg.

Note:

- The needle comes out of the orange tip.
- To avoid an accidental injection, never put your thumb, fingers or hand over the orange tip. If an accidental injection happens, get emergency medical help right away.

Step 2. Administer epinephrine injection, 0.3 mg or epinephrine injection, 0.15 mg

If you are administering epinephrine injection, 0.3 mg or epinephrine injection, 0.15 mg to a young child, hold the leg firmly in place while administering an injection.

Place the orange tip against the middle of the outer thigh (upper leg) at a right angle (perpendicular) to the thigh.
Swing and push the auto-injector firmly until it ‘clicks’.

The click signals that the injection has started.

Hold firmly in place for 3 seconds (count slowly 1,2,3).
The injection is now complete.

Remove the auto-injector from the thigh. The orange tip will extend to cover the needle. If the needle is still visible, do not attempt to reuse it.

Massage the injection area for 10 seconds.

Step 3. Get emergency medical help now. You may need further medical attention. You may need to use a second epinephrine injection, 0.3 mg (auto-injector) or epinephrine injection, 0.15 mg (auto-injector) if symptoms continue or recur.

- Take your used auto-injector with you when you go to see a healthcare provider.
- Tell the healthcare provider that you have received an injection of epinephrine. Show the healthcare provider where you received the injection.
- Give your used epinephrine injection, 0.3 mg (auto-injector) or epinephrine injection, 0.15 mg (auto-injector) to the healthcare provider for inspection and proper disposal.
- Ask for a refill, if needed.

Note:

- Keep the Epinephrine Injection Trainer and the real epinephrine injection, 0.3 mg and epinephrine injection, 0.15 mg Auto-Injectors away from young children. The real epinephrine injection, 0.3 mg and epinephrine injection, 0.15 mg Auto-Injectors and Epinephrine Injection Trainer are not toys. For young children, use of the Epinephrine Injection Trainer and the real epinephrine injection, 0.3 mg and epinephrine injection, 0.15 mg Auto-Injectors should be supervised by an adult.
- A carrying tube is not provided as seen with other products.
- Epinephrine injection, 0.3 mg and epinephrine injection, 0.15 mg are single-dose injectable devices that deliver a fixed dose of epinephrine. The auto-injector cannot be reused. Do not attempt to reuse epinephrine injection after the device has been activated. It is normal for most of the medicine to remain in the auto-injector after the dose is injected. The correct dose has been administered if the orange needle tip is extended and the window is blocked.
- Your epinephrine injection, 0.3 mg (auto-injector) and epinephrine injection, 0.15 mg (auto-injector) may come packaged with an Epinephrine Injection Trainer and separate Epinephrine Injection Trainer Instructions for Use. The Epinephrine Injection Trainer has a grey color. The grey Epinephrine Injection Trainer contains no medicine and no needle. Practice with your Epinephrine Injection Trainer, but always carry your real epinephrine injection, 0.3 mg auto-injector or epinephrine injection, 0.15 mg auto-injector in case of an allergic emergency.
- If you are administering epinephrine injection, 0.3 mg or epinephrine injection, 0.15 mg to a young child, ask your healthcare provider to show you how to (1) hold the young child firmly in place (restrain), (2) with 1 hand, quickly twist the yellow cap off the epinephrine injection, 0.3 mg (auto-injector) or the green cap off the epinephrine injection, 0.15 mg (auto-injector) in the direction of the “twist arrow” to remove it, (3) grasp the auto-injector in your fist with the orange tip (needle end) pointing downward and (4) with your other hand, pull off the blue safety release, and how to properly hold the leg in place while administering a dose.
- Do not try to take the epinephrine injection, 0.3 mg (auto-injector) or epinephrine injection, 0.15 mg (auto-injector) apart.

This Patient Information and Instructions for Use have been approved by the U.S. Food and Drug Administration.

KEEP THIS AND ALL MEDICATIONS OUT OF THE REACH OF CHILDREN.

Manufactured For:
Teva Pharmaceuticals USA, Inc.
North Wales, PA 19454

Rev. C 1/2021

Epinephrine Injection USP, 0.3 mg (Auto-Injector)

Epinephrine Injection USP, 0.3 mg = one dose of 0.3 mg epinephrine USP, 0.3 mg/0.3 mL

Epinephrine Injection USP, 0.15 mg (Auto-Injector)

Epinephrine Injection USP, 0.15 mg = one dose of 0.15 mg epinephrine USP, 0.15 mg/0.3 mL

TevaEpinephrine.com

Register your Epinephrine Injection 0.3 mg (Auto-Injector) or Epinephrine Injection 0.15 mg (Auto-Injector) at www.TevaEpinephrine.com and find out more about:

- Free Epinephrine Injection Auto-Injector Refill Reminder Program. It is important to keep your auto-injector up-to-date.

Register up to 6 Epinephrine Injection 0.3 mg (Auto-Injectors) or Epinephrine Injection 0.15 mg (Auto-Injectors) and receive automatic Refill Reminder Alerts.

- Receive periodic information related to allergies and allergens.
- Instructional Video

For more information about Epinephrine Injection 0.3 mg (Auto-Injector) or Epinephrine Injection 0.15 mg (Auto-Injector) and proper use of the products, call Teva at 1-888-838-2872 or visit www.TevaEpinephrine.com.

Epinephrine Injection Trainer Instructions for Use

In an emergency: Do not use the grey Trainer. Use your real yellow Epinephrine Injection 0.3 mg Auto-Injector or real green Epinephrine Injection 0.15 mg Auto-Injector.

Important Information

- The Trainer label has a grey color.
- The Trainer contains no medicine and no needle.
  Keep the grey Trainer away from young children. The Trainer is not a toy. Young children should only practice with the Trainer under adult supervision.
- Periodically practice with the grey Trainer before an allergic emergency (anaphylaxis) happens to make sure you are able to safely use the real yellow epinephrine injection 0.3 mg auto-injector or real green epinephrine injection 0.15 mg auto-injector in case of an emergency.
- Always carry your real yellow epinephrine injection 0.3 mg auto-injector or real green epinephrine injection 0.15 mg auto-injector in case of an allergic emergency.
- Small parts like the blue safety release may become a choking hazard for children. Put the blue safety release back on the Trainer and reset it immediately after practicing.

The Epinephrine Injection Trainer

Familiarize yourself with this grey Trainer. Practice until you are comfortable using it.

Your grey Trainer:

• Never put your thumb, other fingers, or hand over the orange tip (below grey safety cap).

• The orange tip is where the needle comes out of your epinephrine injection 0.3 mg auto-injector or epinephrine injection 0.15 mg auto-injector.

Practice Instructions

1 Prepare the Trainer for Simulated Injection

- Grasp the grey Trainer in your fist with the orange tip pointing downward and twist off Grey Cap in the direction of “twist arrow”.
- With your other hand, pull off blue safety release.
- Removing the blue safety release unlocks the Trainer.

2 Administer the Trainer Simulation

- If practicing with a young child, hold the leg firmly in place while using the Epinephrine Injection Trainer.
  Ask your healthcare provider to show you how to:
  1. Hold the young child firmly in place (restrain).
  2. With 1 hand, quickly twist the grey cap off the Epinephrine Injection Trainer in the direction of the “twist arrow” to remove it.
  3. Grasp the auto-injector in your fist with the orange tip (needle end) pointing downward.
  4. With your other hand, pull off the blue safety release, and how to properly hold the leg to practice so that you will be prepared before an allergic emergency happens.

- Place the orange tip against the middle of the outer thigh (upper leg) at a right angle (perpendicular) to the thigh.
- Swing and push the Trainer firmly until it ‘clicks’. The click signals that the injection has started.
- Hold firmly in place for 3 seconds (count slowly 1,2,3).
- Remove the Trainer from the thigh and massage the injection area for 10 seconds. The orange tip automatically extends out after use.

Note:

- In an actual emergency, you would need to seek emergency medical help right away.
- The actual auto-injector is made to work through clothing.
- Do not inject into any other part of the body.

3 To reset the Trainer

- Put the blue safety release back on the Trainer.
- Replace Grey Cap.

NOTE: With the real yellow Epinephrine Injection 0.3 mg Auto-Injector or real green Epinephrine Injection 0.15 mg Auto-Injector, the orange tip covers the needle after self-injection to help protect you from accidentally sticking yourself or others.

Practice Session Information

In case of an allergic emergency, use the real yellow Epinephrine Injection 0.3 mg Auto-Injector or real green Epinephrine Injection 0.15 mg Auto-Injector and not the grey Trainer.

Follow instructions above. Repeat as often as needed until you are able to self-inject quickly and correctly.

Reread:

- The Trainer Instructions for Use
- The “Patient Information” that comes with your Epinephrine Injection 0.3 mg Auto-Injector or Epinephrine Injection 0.15 mg Auto-Injector

Train others who could help you in an emergency:

• Your parents, caregivers, and others who may be in a position to administer epinephrine injection 0.3 mg or epinephrine injection 0.15 mg should know how
to help you during an allergic emergency (anaphylaxis). Before an emergency occurs, have them:

- Practice activating the Trainer
- Read these Trainer Instructions and the “Patient Information”

For more information about the Epinephrine Injection 0.3 mg Auto-Injector and Epinephrine Injection 0.15 mg Auto-Injector and the proper use of the products, go to www.TevaEpinephrine.com.

Caution:

Important differences between the Trainer and your real yellow Epinephrine Injection 0.3 mg (Auto-Injector) or real green Epinephrine Injection 0.15 mg (Auto-Injector)

 | Trainer; (Grey) | Epinephrine Injection 0.3 mg; (Yellow) | Epinephrine Injection 0.15 mg; (Green)
Contains medicine? | No | Yes | Yes
Has needle? | No | Yes | Yes
Comes in Carrier Tube? | No | No | No
Color of label | Grey | Yellow | Green
Has expiration date? | No | Yes | Yes
Can be reused? | Yes | No (use only one time) | No (use only one time)
Okay to remove and replace cap and/or safety release? | Yes | No (remove just one time; before use) | No (remove just one time; before use)
Pressure needed to hold against thigh? | Moderate | Strong | Strong

This Trainer Instructions for Use has been approved by the U.S. Food and Drug Administration.

KEEP THIS AND ALL MEDICATIONS OUT OF THE REACH OF CHILDREN.

Manufactured For:
Teva Pharmaceuticals USA, Inc.
North Wales, PA 19454

Rev. D 1/2021

PACKAGE LABEL

DRUG: Epinephrine

GENERIC: Epinephrine

DOSAGE: INJECTION

ADMINSTRATION: INTRAMUSCULAR

NDC: 70518-2283-0

PACKAGING: 0.3 mL in 1 SYRINGE

OUTER PACKAGING: 1 in 1 CONTAINER

OUTER PACKAGING: 2 in 1 CARTON

ACTIVE INGREDIENT(S):

- EPINEPHRINE 0.3mg in 0.3mL

INACTIVE INGREDIENT(S):

- SODIUM CHLORIDE
- SODIUM METABISULFITE
- SODIUM TARTRATE DIHYDRATE
- HYDROCHLORIC ACID
- WATER